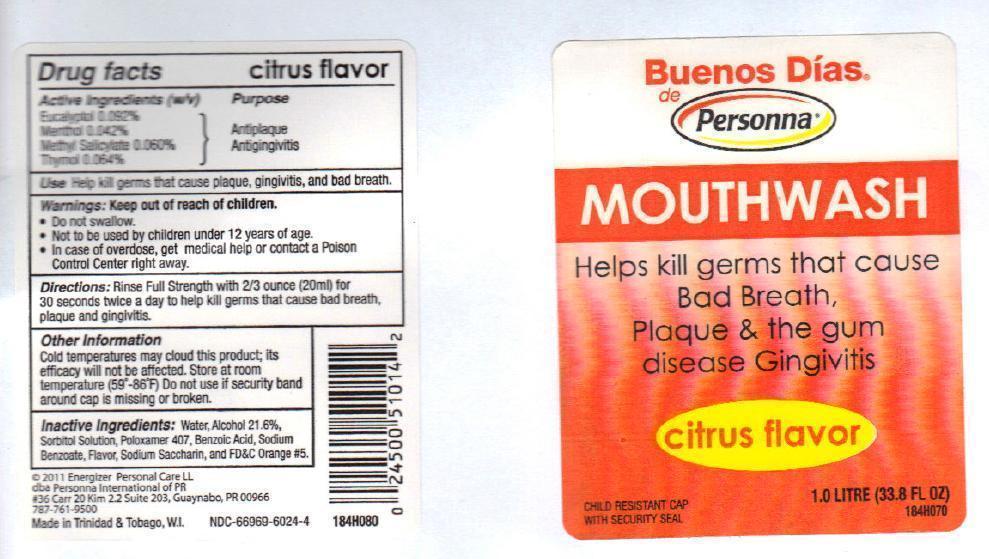 DRUG LABEL: Buenos Dias de Personna
NDC: 66969-6024 | Form: MOUTHWASH
Manufacturer: International Cosmetics Ltd.
Category: otc | Type: HUMAN OTC DRUG LABEL
Date: 20140314

ACTIVE INGREDIENTS: EUCALYPTOL 0.092 g/100 mL; MENTHOL 0.042 g/100 mL; METHYL SALICYLATE 0.060 g/100 mL; THYMOL 0.064 g/100 mL
INACTIVE INGREDIENTS: WATER; ALCOHOL; SORBITOL; POLOXAMER 407; BENZOIC ACID; SODIUM BENZOATE; SACCHARIN SODIUM; SODIUM CITRATE; CITRIC ACID MONOHYDRATE; FD&C YELLOW NO. 6; FD&C RED NO. 40

Buenos Dias de Personna citrus flavour

Active ingredients (W/V)

Eucalyptol 0.092%

Menthol 0.042%

Methyl Salicylate 0.060%

Thymol 0.064%

Purpose

Antiplaque/Antigingivitis

Keep out of reach of children.

In case of overdose, get medical help or contact a Poison Control Center right away.

Uses

Helps kill germs that cause plaque, gingivitis and bad breath.

Warnings

- Do not swallow
- Not to be used by children under 12 years of age

Directions

Rinse Full Strength with 2/3 ounce (20 ml) for 30 seconds twice a day to help kill germs that cause bad breath, plaque and gingivitis.

Other information

- Cold temperature may cloud this product; its efficacy will not be affected. Store at room temperature (59^0-86^0 F).Do not use if security band around cap is missing or broken.

Inactive ingredients

Water, Alcohol 21.6%, Sorbitol Solution, Poloxamer 407, Benzoic Acid, Sodium Benzoate ,Flavour, Sodium Saccharin & FD&C Orange No.5

Distributed By

2011 Energiser Personal Care LL

dba Personna International of PR

#36 Carr 20 Kim 2.2 Suite 203, Guaynabo PR00966

787-761-9500

Made in Trinidad & Tobago,W.I.